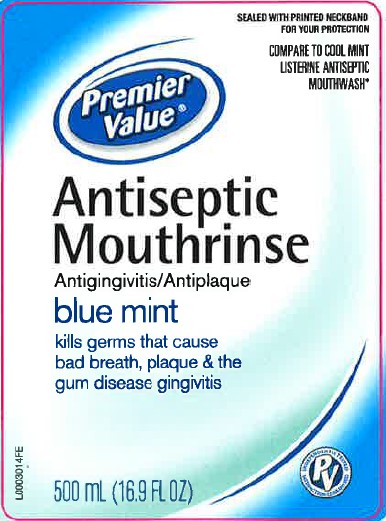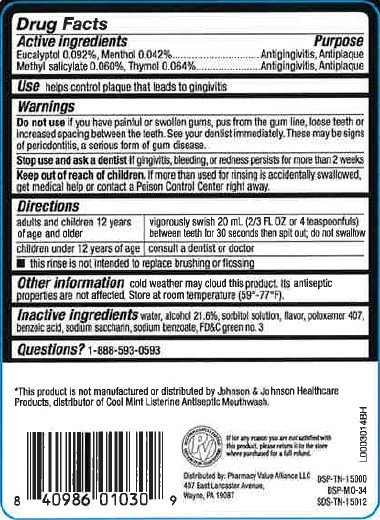 DRUG LABEL: Antispetic
NDC: 68016-664 | Form: MOUTHWASH
Manufacturer: Pharmacy Value Alliance, LLC
Category: otc | Type: HUMAN OTC DRUG LABEL
Date: 20260205

ACTIVE INGREDIENTS: EUCALYPTOL 0.92 mg/1 mL; MENTHOL 0.42 mg/1 mL; METHYL SALICYLATE 0.6 mg/1 mL; THYMOL 0.64 mg/1 mL
INACTIVE INGREDIENTS: WATER; ALCOHOL; SORBITOL; POLOXAMER 407; BENZOIC ACID; SACCHARIN SODIUM; SODIUM BENZOATE; FD&C GREEN NO. 3

Premier Value 664.003/664AT rev 2-AU
Blue Mint Antiseptic Mouthrinse

Active ingredients

Eucalyptol 0.092%

Menthol 0.042%

Methyl salicylate 0.060%

Thymol 0.064%

Purpose

Antigingivitis, antiplaque

use

helps control plaque that leads to gingivitis

Warnings

For this product

Do not use

If you have painful or swollen gums, pus from the gum line, loose teeth or increased spacing between the teeth. See your dentist immediately. These may be signs of periodontitis, a serious form of gum disease.

Stop use and ask a dentist if

gingivitis, bleeding, or redness persists for more than 2 weeks.

Keep out of reach of children.

If more than used for rinsing is accidentally swallowed, get medical help or contact a Poison Control Center right away.

Directions

adults and children 12 years of age and older - vigorously swish 20 mL (2/3 FL OZ or 4 teaspoonfuls) between teeth for 30 seconds then spit out; do not swallow

children under 12 years of age - consult a dentist or doctor

- this rinse is not intended to replace brushing or flossing

Other information

cold weather may cloud this product. Its antiseptic properties are not affected. Store at room temperature (59°-77°F).

Inactive ingredients

water, alcohol 21.6%, sorbitol solution, flavor, poloxamer 407, benzoic acid, sodium saccharin, sodium benzoate, FD&C green no.3

Disclaimers

*This product is not manufactured or distributed by Johnson & Johnson Healthcare Products, distributor of Cool Mint Listerine Antiseptic mouthwash.

Adverse Reactions

If for any reason you are not satisfied with this product, please return it to the store where purchased for a full refund.

Distributed by: Pharmacy Value Alliance LLC

407 East Lancaster Avenue,

Wayne, PA 19087

DSP-TN-15000

DSP-MO-34

SDS-TN-15012

Principal Display Panel

SEALED WITH PRINTED NECKBAND FOR YOUR PROTECTION

COMPARE TO COOL MINT LISTERINE ANTSEPTIC MOUTHWASH*

Premier Value®

Antiseptic

Mouthrinse

Antigingivitis/Antiplaque

blue mint

kils germs that cause bad breath, plaque & the gum disease gingivitis

PV

500 mL (16.9 FL OZ)